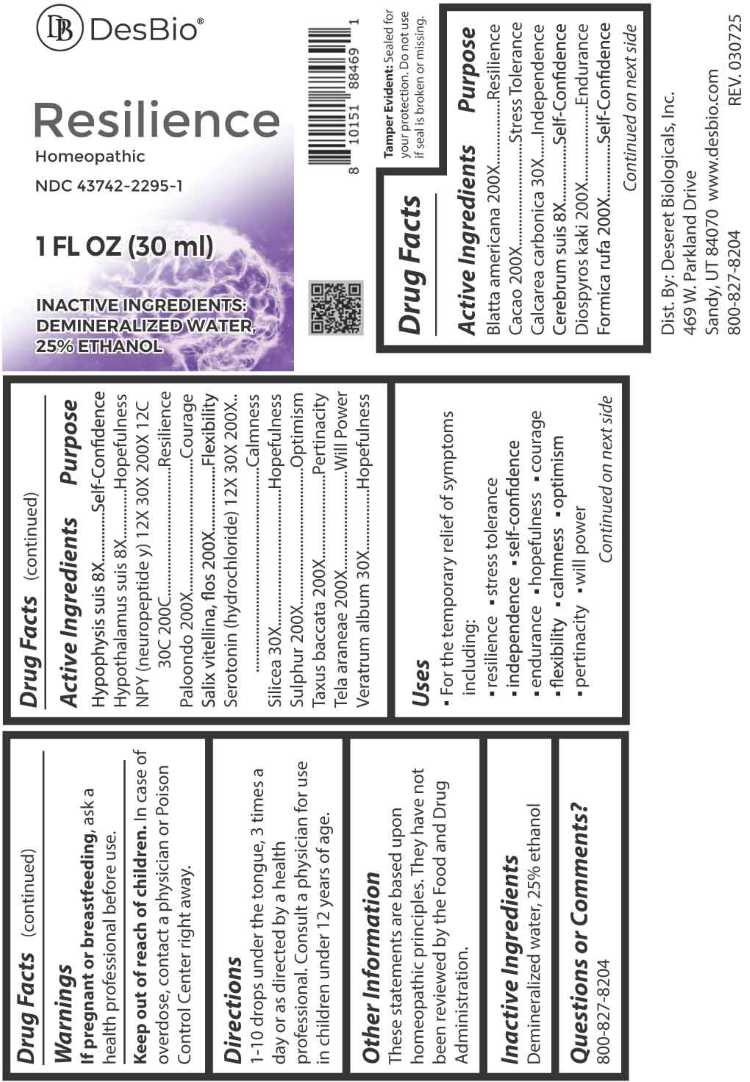 DRUG LABEL: Resilience
NDC: 43742-2295 | Form: LIQUID
Manufacturer: Deseret Biologicals, Inc.
Category: homeopathic | Type: HUMAN OTC DRUG LABEL
Date: 20260226

ACTIVE INGREDIENTS: SUS SCROFA CEREBRUM 8 [hp_X]/1 mL; SUS SCROFA HYPOTHALAMUS 8 [hp_X]/1 mL; SUS SCROFA PITUITARY GLAND 8 [hp_X]/1 mL; SEROTONIN HYDROCHLORIDE 12 [hp_X]/1 mL; NEUROPEPTIDE Y 12 [hp_X]/1 mL; OYSTER SHELL CALCIUM CARBONATE, CRUDE 30 [hp_X]/1 mL; SILICON DIOXIDE 30 [hp_X]/1 mL; VERATRUM ALBUM ROOT 30 [hp_X]/1 mL; PERIPLANETA AMERICANA 200 [hp_X]/1 mL; COCOA 200 [hp_X]/1 mL; PERSIMMON 200 [hp_X]/1 mL; FORMICA RUFA 200 [hp_X]/1 mL; LARREA TRIDENTATA LEAF 200 [hp_X]/1 mL; SULFUR 200 [hp_X]/1 mL; TAXUS BACCATA FRUIT 200 [hp_X]/1 mL; BOMBYX MORI FIBER 200 [hp_X]/1 mL; SALIX ALBA FLOWERING TOP 200 [hp_X]/1 mL
INACTIVE INGREDIENTS: WATER; ALCOHOL

DRUG FACTS:

ACTIVE INGREDIENTS:

Blatta Americana 200X, Cacao 200X, Calcarea Carbonica 30X, Cerebrum Suis 8X, Diospyros Kaki 200X, Formica Rufa 200X, Hypophysis Suis 8X, Hypothalamus Suis 8X, NPY (Neuropeptide Y) 12X, 30X, 200X, 12C, 30C, 200C, Paloondo 200X, Salix Vitellina, Flos 200X, Serotonin (Hydrochloride) 12X, 30X, 200X, Silicea 30X, Sulphur 200X, Taxus Baccata 200X, Tela Araneae 200X, Veratrum Album 30X.

PURPOSE:

Blatta Americana - Resilience, Cacao – Stress Tolerance, Calcarea Carbonica - Independence, Cerebrum Suis – Self-Confidence, Diospyros Kaki - Endurance, Formica Rufa – Self-Confidence, Hypophysis Suis – Self-Confidence, Hypothalamus Suis - Hopefulness, NPY (Neuropeptide Y) - Resilience, Paloondo - Courage, Salix Vitellina, Flos - Flexibility, Serotonin (Hydrochloride) - Calmness, Silicea - Hopefulness, Sulphur - Optimism, Taxus Baccata - Pertinacity, Tela Araneae – Will Power, Veratrum Album - Hopefulness

USES:

• For the temporary relief of symptoms including:

• resilience • stress tolerance • independence • self-confidence • endurance • hopefulness

• courage • flexibility • calmness • optimism • pertinacity • will power

These statements are based upon homeopathic principles. They have not been reviewed by the Food and Drug Administration.

WARNINGS:

If pregnant or breastfeeding, ask a health professional before use.

Keep out of reach of children. In case of overdose, contact a physician or Poison Control Center right away.

Tamper Evident: Sealed for your protection. Do not use if seal is broken or missing.

KEEP OUT OF REACH OF CHILDREN:

In case of overdose, contact a physician or Poison Control Center right away.

DIRECTIONS:

1-10 drops under the tongue, 3 times a day or as directed by a health professional. Consult a physician for use in children under 12 years of age.

INACTIVE INGREDIENTS:

Demineralized water, 25% ethanol

QUESTIONS:

Dist. By: Deseret Biologicals, Inc.

469 W. Parkland Drive

Sandy, UT 84070

www.desbio.com

800-827-8204

PACKAGE LABEL DISPLAY:

DesBio

Resilience

Homeopathic

NDC 43742-2295-1

1 FL OZ (30ml)